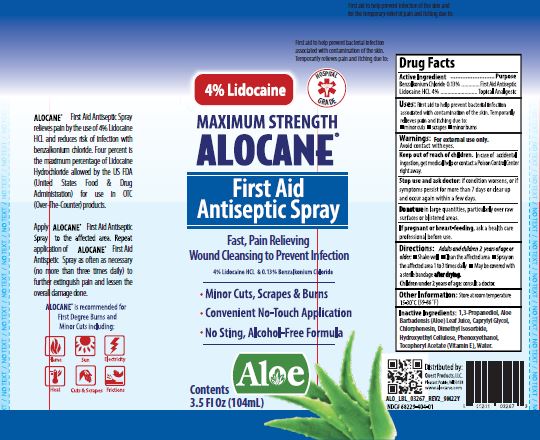 DRUG LABEL: Alocane Plus
NDC: 68229-404 | Form: GEL
Manufacturer: Quest Products, Inc.
Category: otc | Type: HUMAN OTC DRUG LABEL
Date: 20241105

ACTIVE INGREDIENTS: LIDOCAINE HYDROCHLORIDE 4 g/100 mL; BENZALKONIUM CHLORIDE 0.13 g/100 mL
INACTIVE INGREDIENTS: PROPANEDIOL; ALOE VERA LEAF; DIMETHYL ISOSORBIDE; HYDROXYETHYL CELLULOSE (5500 MPA.S AT 2%); PHENOXYETHANOL; CAPRYLYL GLYCOL; CHLORPHENESIN; .ALPHA.-TOCOPHEROL ACETATE; WATER

Alocane® First Aid Antiseptic

Drug Facts

Active Ingredients

Benzalkonium Chloride 0.13%

Lidocaine HCl 4.0%

Purpose

First Aid Antiseptic

Topical Analgesic

Uses

First Aid to help prevent bacterial infection associated with contamination of the skin. Temporarily relieves pain and itching due to:

- minor cuts
- scrapes
- minor burns

Warnings

For external use only. Avoid contact with eyes.

Keep out of reach of children. In case of accidental ingestion, get medical help or contact a Poison Control Center right away.

Stop use and ask doctor: if condition worsens, or if symptoms persist for more than 7 days or clear up and occur again within a few days.

Stop Use and ask doctor

if condition worsens, or if symptoms persist for more than 7 days or clear up and occur again within a few days.

Do not use:

in large quantities, particularly over raw surfaces or blistered areas.

If pregnant or breast-feeding

ask a health care professional before use.

Directions:

Adults and children 2 years of age or older:

- Shake well
- Clean the affected area
- Spray on the affected area 1 to 3 times daily
- May be covered with a sterile bandage after drying

Children under 2 years of age: consult a doctor

Other Information

Store at room temperature of 15° - 30°C (59° - 86°F)

Inactive Ingredients

1,3-Propanediol, Aloe Barbadensis (Aloe) Leaf Juice, Caprylyl Glycol, Chlorphenesin, Dimethyl Isosorbide, Hydroxyethyl Cellulose, Phenoxyethanol, Tocopheryl Acetate (Vitamin E), Water.